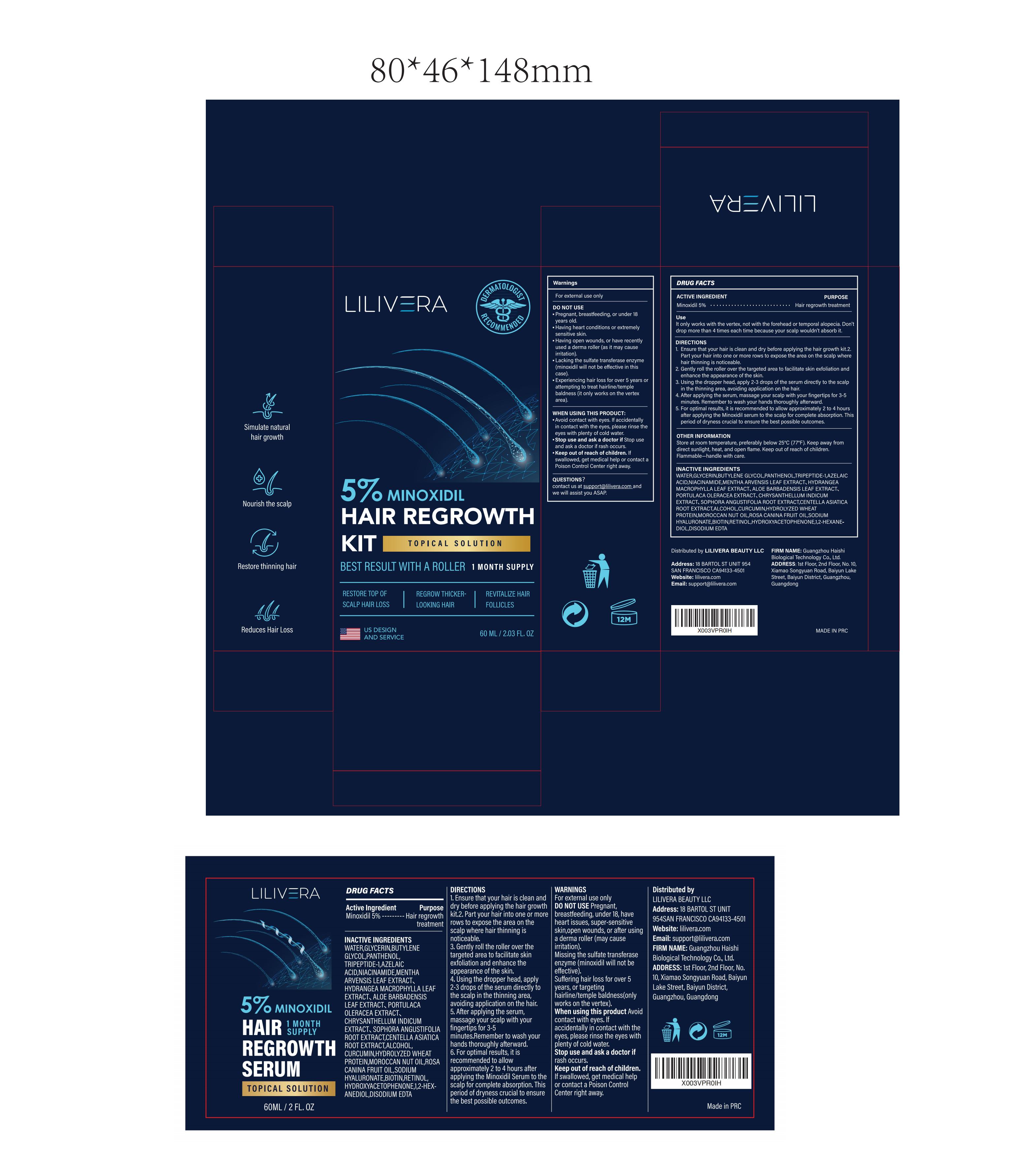 DRUG LABEL: LILIVERA Hair Regrowth Kit
NDC: 60771-0012 | Form: LIQUID
Manufacturer: Guangzhou Haishi Biological Technology Co., Ltd.
Category: otc | Type: HUMAN OTC DRUG LABEL
Date: 20250417

ACTIVE INGREDIENTS: MINOXIDIL 5 g/100 mL
INACTIVE INGREDIENTS: BUTYLENE GLYCOL; PANTHENOL; TRIPEPTIDE-1; MENTHA ARVENSIS LEAF; GLYCERIN; NIACINAMIDE; AZELAIC ACID

LILIVERA HAIR REGROWTH KIT

Active ingredients

Minoxidil 5%

Purpose

Hair regrowth treatment

Uses

lt only works with the vertex, not with the forehead or temporal alopecia.

Don't drop more than 4 times each time because your scalp wouldn't absorb it.

Warnings

For external use only.

Stop use and ask a doctor if

rash occurs.

Do not use

Pregnant, breastfeeding, under 18, have heart issues, super-sensitive skin,open wounds, or after using a derma roller (may cause irritation).
Missing the sulfate transferase enzyme (minoxidil will not be effective).
Suffering hair loss for over 5 years, or targeting hairline/temple baldness(only works on the vertex).

When using this product

Avoid contact with eyes. If accidentally in contact with the eyes, please rinse the eyes with plenty of cold water.

Keep out of reach of children.

If swallowed, get medical help or contact a Poison Control Center right away.

Dosage

Don't drop more than 4 times each time because your scalp wouldn't absorb it.

Inactive ingredients

WATER 59.425%
GLYCERIN 5%
BUTYLENE GLYCOL 5%
PANTHENOL 1%
TRIPEPTIDE-1 2%
AZELAIC ACID 2%
NIACINAMIDE 2%
MENTHA ARVENSIS LEAF EXTRACT 0.83%
HYDRANGEA MACROPHYLLA LEAF EXTRACT 0.83%
ALOE BARBADENSIS LEAF EXTRACT 0.83%
PORTULACA OLERACEA EXTRACT 0.83%
CHRYSANTHELLUM INDICUM EXTRACT 0.83%
SOPHORA ANGUSTIFOLIA ROOT EXTRACT 0.85%
CENTELLA ASIATICA ROOT EXTRACT 2%
ALCOHOL 3%
CURCUMIN 0.5%
HYDROLYZED WHEAT PROTEIN 2%
MOROCCAN NUT OIL 2%
ROSA CANINA FRUIT OIL 1%
SODIUM HYALURONATE 1%
BIOTIN 1%
RETINOL 0.025%
HYDROXYACETOPHENONE 0.5%
1,2-HEXANEDIOL 0.5%
DISODIUM EDTA 0.05%